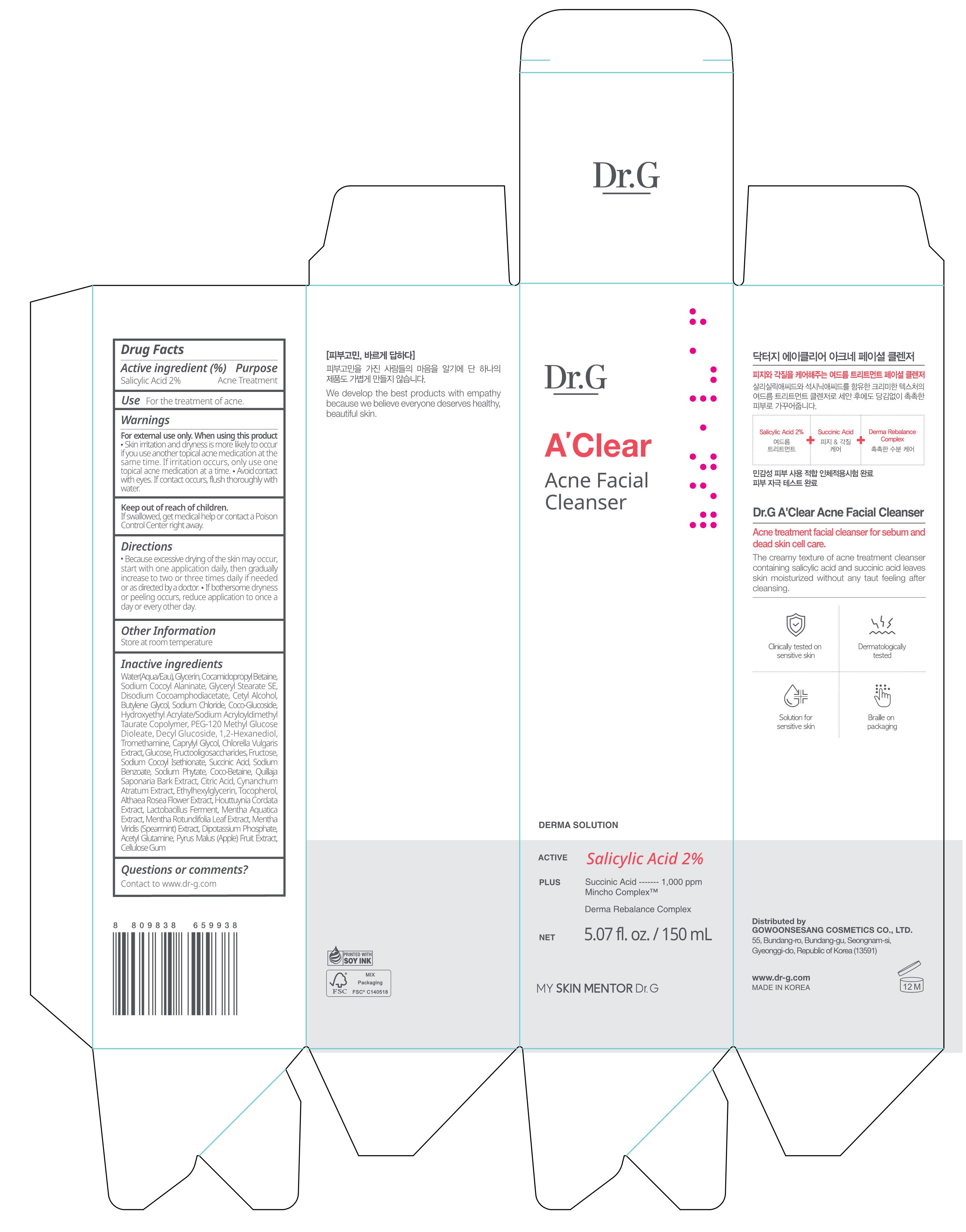 DRUG LABEL: Dr.G A CLEAR ACNE FACIAL CLEANSER
NDC: 51621-410 | Form: CREAM
Manufacturer: GOWOONSESANG COSMETICS CO., LTD.
Category: otc | Type: HUMAN OTC DRUG LABEL
Date: 20250320

ACTIVE INGREDIENTS: SALICYLIC ACID 2 g/100 mL
INACTIVE INGREDIENTS: SODIUM PHYTATE; DIBASIC POTASSIUM PHOSPHATE; PEG-120 METHYL GLUCOSE DIOLEATE; FRUCTOSE; CETYL ALCOHOL; COCO-BETAINE; CITRIC ACID; ETHYLHEXYLGLYCERIN; SODIUM CHLORIDE; SODIUM BENZOATE; DECYL GLUCOSIDE; TROMETHAMINE; GLUCOSE; GLYCERIN; WATER; CAPRYLYL GLYCOL; HYDROXYETHYL ACRYLATE/SODIUM ACRYLOYLDIMETHYL TAURATE COPOLYMER (45000 MPA.S AT 1%); SODIUM COCOYL ALANINATE; CELLULOSE GUM; DISODIUM COCOAMPHODIACETATE; SODIUM COCOYL ISETHIONATE; TOCOPHEROL; ALCEA ROSEA FLOWER; MENTHA X ROTUNDIFOLIA LEAF; VINCETOXICUM ATRATUM WHOLE; COCO-GLUCOSIDE; SUCCINIC ACID; BUTYLENE GLYCOL; 1,2-HEXANEDIOL; CHLORELLA VULGARIS; ACEGLUTAMIDE; MENTHA SPICATA; COCAMIDOPROPYL BETAINE; QUILLAJA SAPONARIA BARK; PYRUS MALUS (APPLE) FRUIT; GLYCERYL STEARATE SE; HOUTTUYNIA CORDATA FLOWERING TOP

Active ingredient

Salicylic Acid 2%

Purpose

Acne Treatment

Use

For the treatment of acne.

Warnings

For external use only. When using this product

- Skin irritation and dryness is more likely to occur if you use another topical acne medication at the same time. If irritation occurs, only use one topical acne medication at a time.
- Avoid contact with eyes. If contact occurs, flush thoroughly with water.

Keep out of reach of children.

If swallowed, get medical help or contact a Poison Control Center right away.

Directions

- Because excessive drying of the skin may occur, start with one application daily, then gradually increase to two or three times daily if needed or as directed by a doctor.
- If bothersome dryness or peeling occurs, reduce application to once a day or every other day.

Other Information

Store at room temperature

Inactive ingredients

Water(Aqua/Eau), Glycerin, Cocamidopropyl Betaine, Sodium Cocoyl Alaninate, Glyceryl Stearate SE, Disodium Cocoamphodiacetate, Cetyl Alcohol, Butylene Glycol, Sodium Chloride, Coco-Glucoside, Hydroxyethyl Acrylate/Sodium Acryloyldimethyl Taurate Copolymer, PEG-120 Methyl Glucose Dioleate, Decyl Glucoside, 1,2-Hexanediol, Tromethamine, Caprylyl Glycol, Chlorella Vulgaris Extract, Glucose, Fructooligosaccharides, Fructose, Sodium Cocoyl Isethionate, Succinic Acid, Sodium Benzoate, Sodium Phytate, Coco-Betaine, Quillaja Saponaria Bark Extract, Citric Acid, Cynanchum Atratum Extract, Ethylhexylglycerin, Tocopherol, Althaea Rosea Flower Extract, Houttuynia Cordata Extract, Lactobacillus Ferment, Mentha Aquatica Extract, Mentha Rotundifolia Leaf Extract, Mentha Viridis (Spearmint) Extract, Dipotassium Phosphate, Acetyl Glutamine, Pyrus Malus (Apple) Fruit Extract, Cellulose Gum

Questions or comments?

Contact to www.dr-g.com